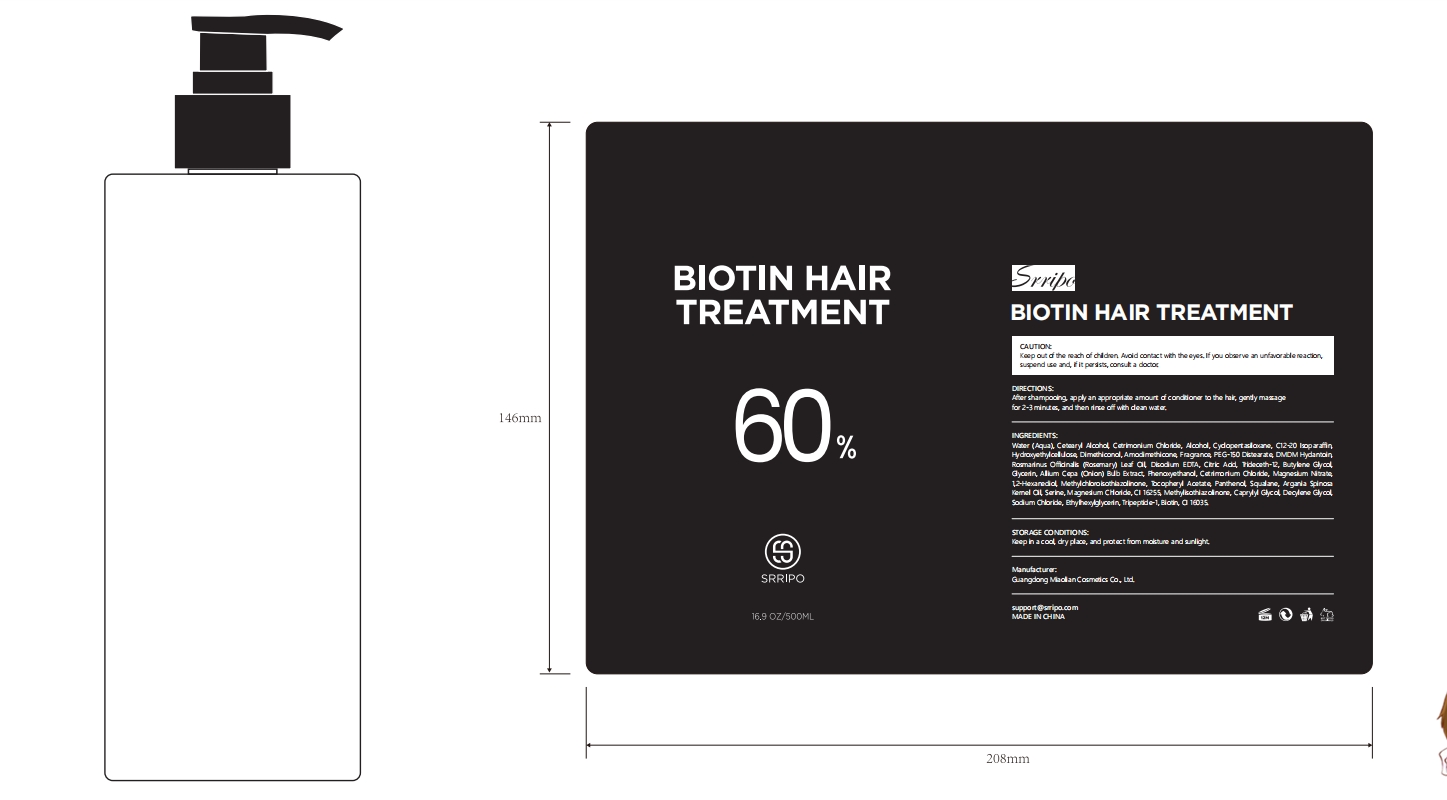 DRUG LABEL: Srripo Biotin Hair Treatment
NDC: 84507-022 | Form: SHAMPOO
Manufacturer: Guangdong Miaolian Cosmetics Co., Ltd.
Category: otc | Type: HUMAN OTC DRUG LABEL
Date: 20240911

ACTIVE INGREDIENTS: BUTYLENE GLYCOL 1.6 mg/100 mL
INACTIVE INGREDIENTS: WATER

DOSAGE AND ADMINISTRATION

After shampooing, apply an appropriate amount of conditioner to the hair gently massage
for 2-3 minutes, and then rinse off with clean water.

WARNINGS

Keep out of the reach of children. Avoid contact with the eyes. If you observe an unfavorable reaction, suspend use and, if it persists, consult a doctor.

INACTIVE INGREDIENT

Water...

INDICATIONS AND USAGE

Deeply moisturizes hair. When used with Biotin Shampoo, it helps improve dryness, repair damage,and reduce split ends and breakage.

Keep out of the reach of children.

PURPOSE

Deeply moisturizes hair.